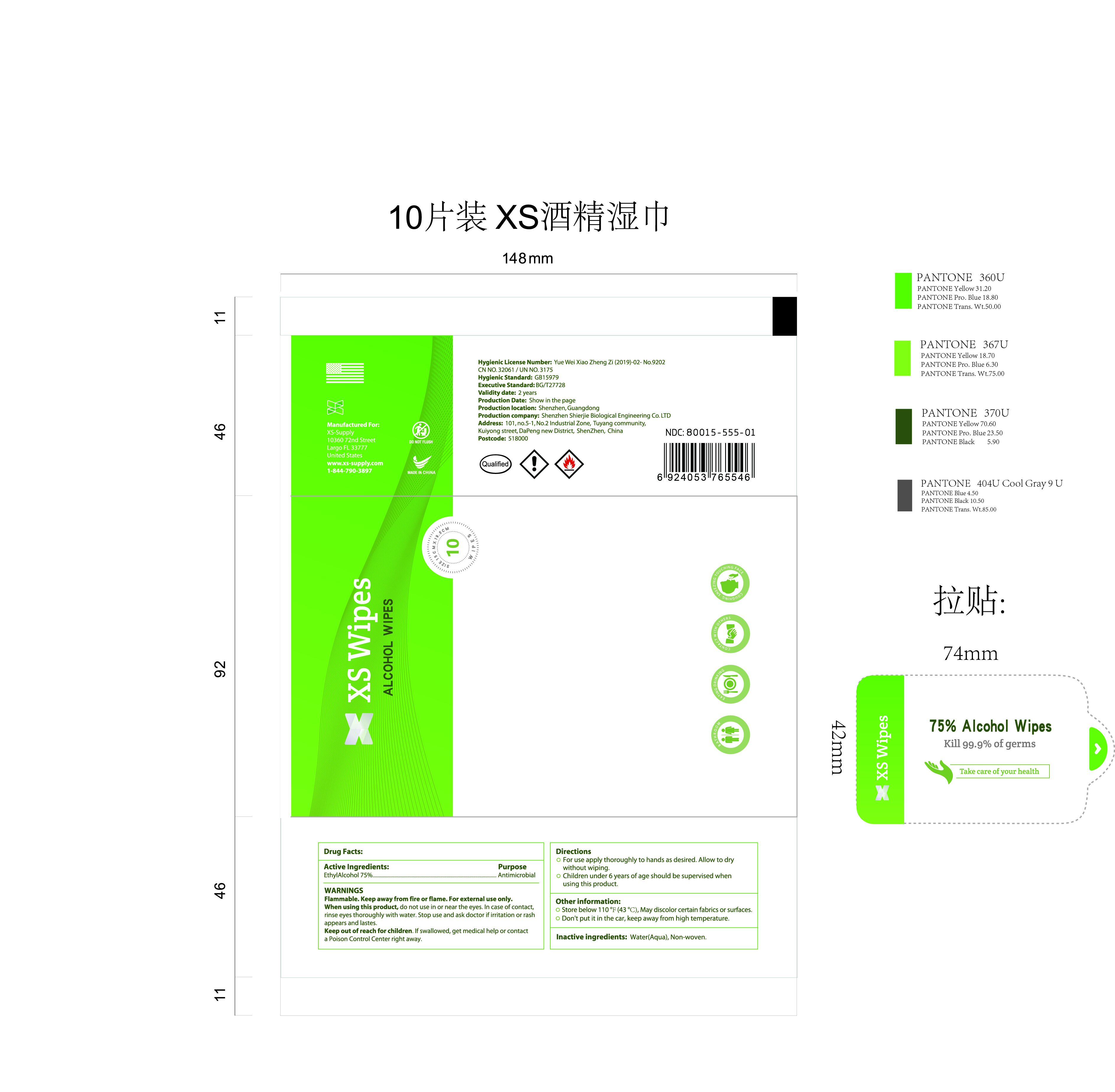 DRUG LABEL: XS 75%Alcohol wipes
NDC: 43116-025 | Form: CLOTH
Manufacturer: Shenzhen Shierjie Biological Engineering Co., LTD
Category: otc | Type: HUMAN OTC DRUG LABEL
Date: 20200902

ACTIVE INGREDIENTS: ALCOHOL 75 mL/100 1
INACTIVE INGREDIENTS: WATER

43116-025
XS 75%Alcohol wipes

Active Ingredient

EthylAlcohol 75%.

Purpose

Antimicrobial

Uses

/

Warnings

Flammable. Keep away from fire or flame. For external use only.

When using this product, do not use in or near the eyes. In case of contact, rinse eyes thoroughly with water. Stop use and ask doctor if irritation or rash appears and lastes.

Keep out of reach for children. If swallowed, get medical help or contact a Poison Control Center right away.

DO NOT USE

/

When using this product, do not use in or near the eyes. In case of contact, rinse eyes thoroughly with water. Stop use and ask doctor if irritation or rash appears and lastes.

Keep out of reach for children. If swallowed, get medical help or contact a Poison Control Center right away.

STOP USE

/

KEEP OUT OF REACH OF CHILDREN

Keep out of reach for children. If swallowed, get medical help or contact a Poison Control Center right away.

Directions

For use apply thoroughly to hands as desired. Allow to dry without wiping.
Children under 6 years of age should be supervised when using this product.

Other information

Store below 110 °F (43 °C), May discolor certain fabrics or surfaces.
Don't put it in the car, keep away from high temperature.

Inactive ingredients

Water(Aqua), Non-woven.